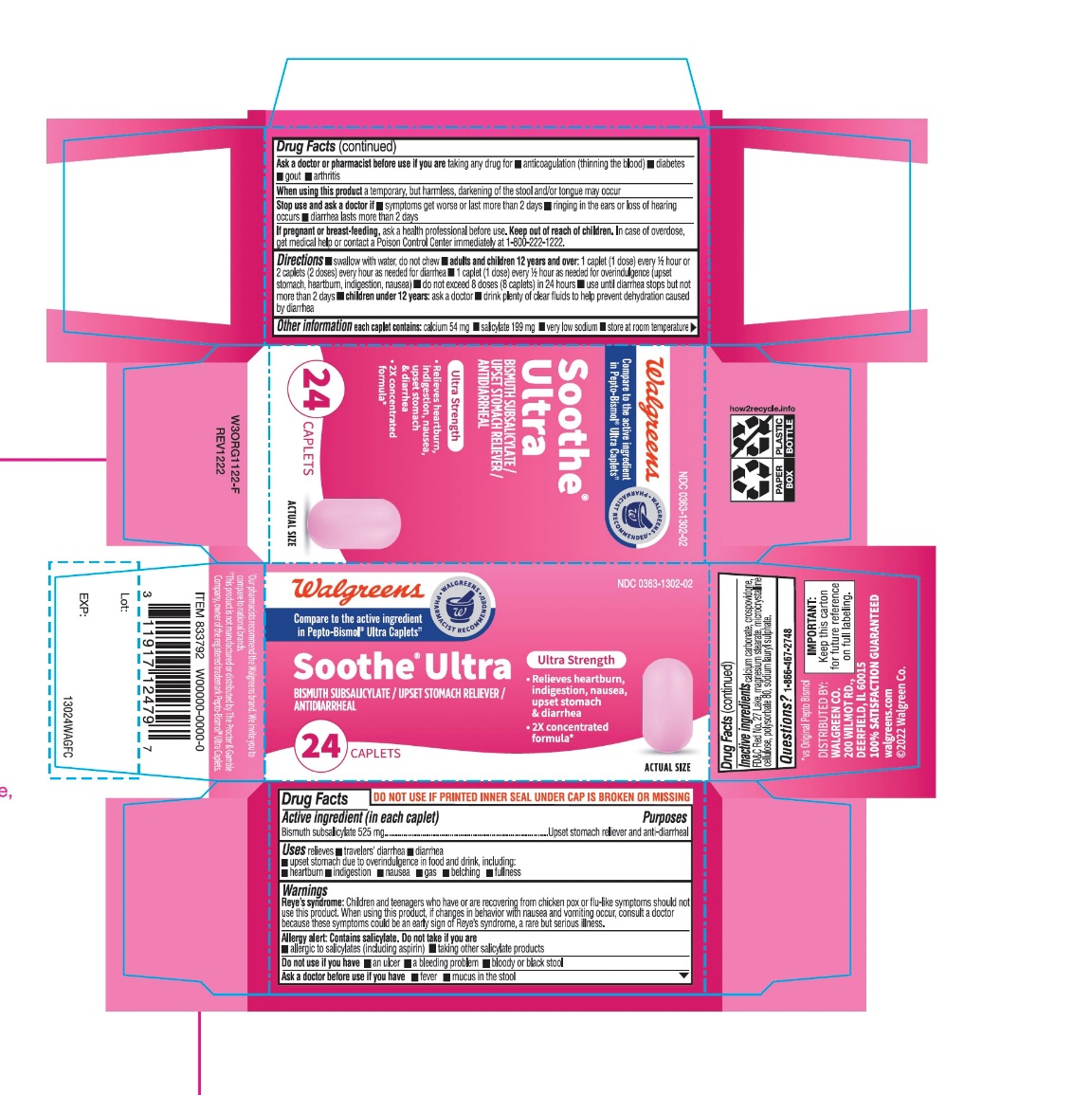 DRUG LABEL: Ultra Strength digestive relief
NDC: 0363-1302 | Form: TABLET
Manufacturer: WALGREENS CO.
Category: otc | Type: HUMAN OTC DRUG LABEL
Date: 20251126

ACTIVE INGREDIENTS: BISMUTH SUBSALICYLATE 525 mg/1 1
INACTIVE INGREDIENTS: CALCIUM CARBONATE; CROSPOVIDONE (120 .MU.M); D&C RED NO. 27; MAGNESIUM STEARATE; MICROCRYSTALLINE CELLULOSE; POLYSORBATE 80; SODIUM LAURYL SULFATE

Ultra Strength Digestive Relief 24 Caplets

Drug Facts

Active ingredient (in each caplet)

Bismuth Subsalicylate 525 mg

Purpose

Upset stomach reliever and anti-diarrheal

Uses

relieves

- travelers' diarrhea
- diarrhea
- upset stomach due to overindulgence in food and drink, including:
  - heartburn
  - indigestion
  - nausea
  - gas
  - belching
  - fullness

Warnings

Reye's syndrome

Children and teenagers who have or are recovering from chicken pox or flu-like symptoms should not use this product. When using this product, if changes in behavior with nausea and vomiting occur, consult a doctor because these symptoms could be an early sign of Reye's syndrome, a rare but serious illness.

Allergy alert

Contains salicylate. Do not take if you are

- allergic to salicylates (including aspirin)
- taking other salicylate products

Do not use ifyou have

- an ulcer
- a bleeding problem
- bloody or black stool

Ask a doctor before use if you have

- fever
- mucus in the stool

Ask a doctor or pharmacist before use if you aretaking any drug for

- anticoagulation (thinning the blood)
- diabetes
- gout
- arthritis

WHEN USING

When using this producta temporary, but harmless, darkening of the stool and/or tongue may occur

Stop use and ask a doctor if

- symptoms get worse or last more than 2 days
- ringing in the ears or loss of hearing occurs
- diarrhea lasts more than 2 days

PREGNANCY OR BREAST FEEDING

If pregnant or breast feeding,ask a health professional before use.

Keep out of reach of children.In case of overdose, get medical help or contact a Poison Control Center immediately at 1-800-222-1222.

Directions

- swallow with water, do not chew
- adults and children 12 years and over:1 caplet (1 dose) every ½ hour or 2 caplets (2 doses) every hour as needed for diarrhea
- 1 caplet (1 dose) every ½ hour as needed for overindulgence (upset stomach, heartburn, indigestion, nausea)
- do not exceed 8 doses (8 caplets) in 24 hours
- use until diarrhea stops but not more than 2 days
- children under 12 years: ask a doctor
- drink plenty of clear fluids to help prevent dehydration caused by diarrhea

Other information

- each caplet contains:calcium 54 mg
- salicylate 199 mg
- very low sodium
- store at room temperature

Inactive ingredients

calcium carbonate, crospovidone, FD&C Red No. 27 Lake, magnesium stearate, microcrystalline cellulose, polysorbate 80, sodium lauryl sulphate.

Questions?

1-866-467-2748

PRINCIPAL DISPLAY PANEL - 24 Caplet Carton

Compare to the active Ingredient in Pepto-Bismosol® Ultra Caplets*

NDC 0363-1302-02

Ultra Strength

Digestive Relief

Bismuth Subsalicylate
Upset Stomach Reliever/Antidiarrheal

5 Symptom Digestive Relief

- Heartburn
- Indigestion
- Nausea
- Upset Stomach
- Diarrhea

2X CONCENTRATED FORMULA

24 Caplets